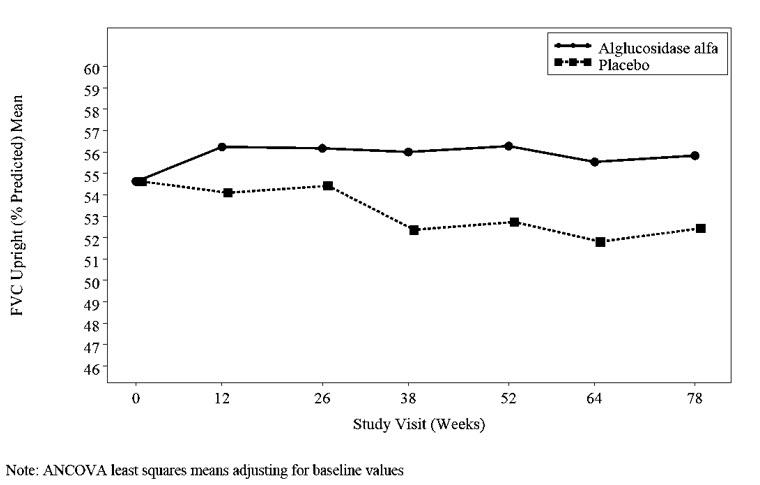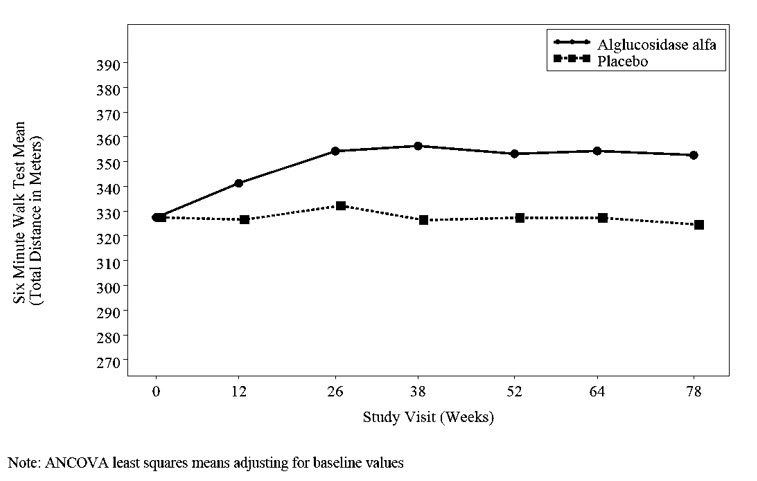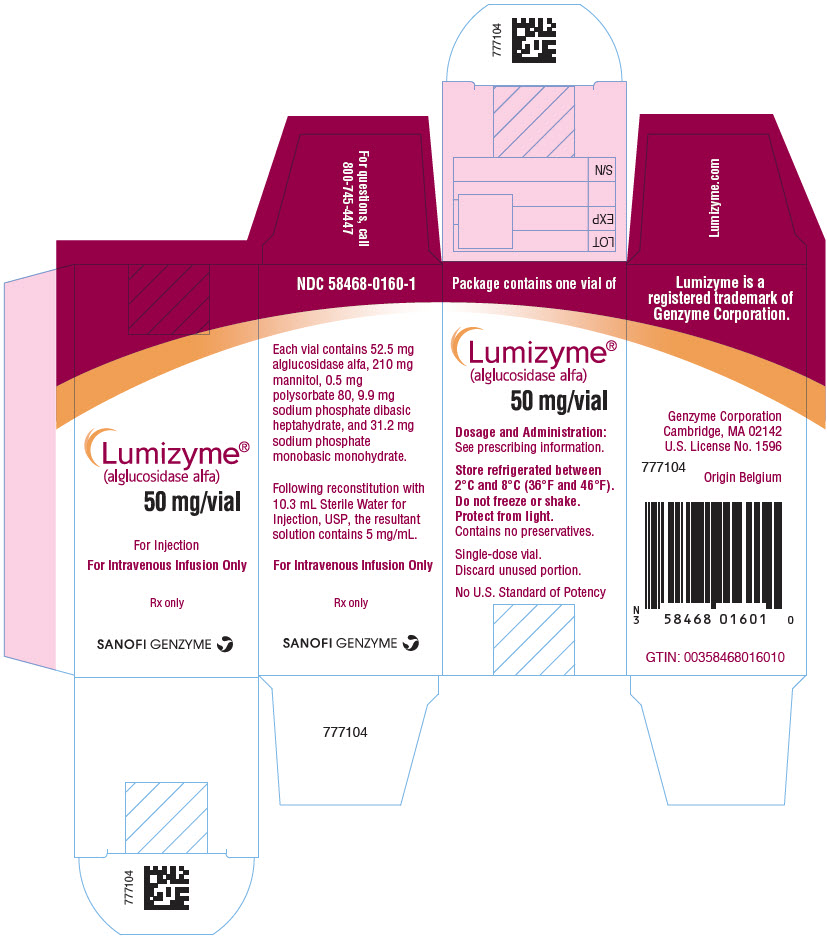 DRUG LABEL: Lumizyme
NDC: 58468-0160 | Form: INJECTION, POWDER, FOR SOLUTION
Manufacturer: Genzyme Corporation
Category: prescription | Type: HUMAN PRESCRIPTION DRUG LABEL
Date: 20250110

ACTIVE INGREDIENTS: ALGLUCOSIDASE ALFA 5 mg/1 mL
INACTIVE INGREDIENTS: MANNITOL 20 mg/1 mL; SODIUM PHOSPHATE, MONOBASIC, MONOHYDRATE 2.97 mg/1 mL; SODIUM PHOSPHATE, DIBASIC, HEPTAHYDRATE 0.94 mg/1 mL; POLYSORBATE 80 0.05 mg/1 mL

HIGHLIGHTS OF PRESCRIBING INFORMATION

These highlights do not include all the information needed to use LUMIZYME safely and effectively. See full prescribing information for LUMIZYME.
LUMIZYME® (alglucosidase alfa), for injection, for intravenous use
Initial U.S. Approval: 2010

WARNING: HYPERSENSITIVITY REACTIONS INCLUDING ANAPHYLAXIS, IMMUNE-MEDIATED REACTIONS, and RISK OF ACUTE CARDIORESPIRATORY FAILURE

See full prescribing information for complete boxed warning.

Hypersensitivity Reactions Including Anaphylaxis

Anaphylaxis has occurred during the early course of enzyme replacement therapy and after extended duration of therapy. Initiate LUMIZYME in a healthcare setting with appropriate medical monitoring and support measures, including access to cardiopulmonary resuscitation equipment. If a severe hypersensitivity reaction (e.g., anaphylaxis) occurs, discontinue LUMIZYME and immediately initiate appropriate medical treatment, including use of epinephrine. (5.1)

Immune-Mediated Reactions

Immune-mediated reactions presenting as proteinuria, nephrotic syndrome, and necrotizing skin lesions have occurred in some patients following LUMIZYME treatment. Monitor patients for the development of systemic immune-mediated reactions involving skin and other organs while receiving LUMIZYME. (5.3)

Risk of Acute Cardiorespiratory Failure

Infantile-onset Pompe disease (IOPD) patients with compromised cardiac or respiratory function may be at risk of serious acute exacerbation of their cardiac or respiratory compromise due to fluid overload and require additional monitoring. (5.4)

RECENT MAJOR CHANGES

Boxed Warning | 3/2024, 12/2024
Dosage and Administration (2.1, 2.2) | 3/2024, 12/2024
Warnings and Precautions (5.1, 5.2, 5.6) | 3/2024, 12/2024
Warnings and Precautions, Monitoring (5.7) | Removed 12/2024

1 INDICATIONS AND USAGE

LUMIZYME® is a hydrolytic lysosomal glycogen-specific enzyme indicated for patients with Pompe disease (GAA deficiency). (1)

2 DOSAGE AND ADMINISTRATION

- Administration of LUMIZYME should be supervised by a healthcare provider knowledgeable in the management of hypersensitivity reactions including anaphylaxis. (2.1)
- Recommended dosage is 20 mg/per kg body weight administered every 2 weeks as an intravenous infusion. The initial infusion rate should be no more than 1 mg/kg/hour (2.2)
- Reconstitute and dilute LUMIZYME prior to use. (2.3)
- See full prescribing information for storage of the reconstituted and diluted product and administration instructions (2.4, 2.5)

3 DOSAGE FORMS AND STRENGTHS

For injection: 50 mg of LUMIZYME as lyophilized powder in a single-dose vial for reconstitution. (3)

4 CONTRAINDICATIONS

None. (4)

5 WARNINGS AND PRECAUTIONS

- Infusion-Associated Reactions (IARs): If an IAR occurs, decreasing the infusion rate, temporarily stopping the infusion, and/or administration of antihistamines and/or antipyretics may ameliorate the symptoms. (5.2)
- Risk of Cardiac Arrhythmia and Sudden Cardiac Death during General Anesthesia for Central Venous Catheter Placement: Caution should be used when administering general anesthesia for the placement of a central venous catheter intended for LUMIZYME infusion. (5.5)
- Risk of Developing Anti-alglucosidase Alfa Antibodies: Patients with IOPD should have a cross-reactive immunologic material (CRIM) assessment early in their disease course and be managed by a clinical specialist knowledgeable in immune tolerance induction in Pompe disease. (5.6)

6 ADVERSE REACTIONS

The most frequently reported adverse reactions (≥5%) in clinical trials were hypersensitivity reactions and included: anaphylaxis, rash, pyrexia, flushing/feeling hot, urticaria, headache, hyperhidrosis, nausea, cough, decreased oxygen saturation, tachycardia, tachypnea, chest discomfort, dizziness, muscle twitching, agitation, cyanosis, erythema, hypertension/increased blood pressure, pallor, rigors, tremor, vomiting, fatigue, and myalgia. (6.1)

To report SUSPECTED ADVERSE REACTIONS, contact Genzyme at 1-800-633-1610, option 1 or FDA at 1-800-FDA-1088 or www.fda.gov/medwatch.

FULL PRESCRIBING INFORMATION

WARNING: HYPERSENSITIVITY REACTIONS INCLUDING ANAPHYLAXIS, IMMUNE-MEDIATED REACTIONS, and RISK OF ACUTE CARDIORESPIRATORY FAILURE

Hypersensitivity Reactions Including Anaphylaxis

Patients treated with enzyme replacement therapies have experienced life-threatening hypersensitivity reactions, including anaphylaxis. Anaphylaxis has occurred during the early course of enzyme replacement therapy and after extended duration of therapy. Initiate LUMIZYME in a healthcare setting with appropriate medical monitoring and support measures, including access to cardiopulmonary resuscitation equipment. If a severe hypersensitivity reaction (e.g., anaphylaxis) occurs, discontinue LUMIZYME and immediately initiate appropriate medical treatment, including use of epinephrine. Inform patients of the symptoms of life-threatening hypersensitivity reactions, including anaphylaxis and to seek immediate medical care should symptoms occur [see Warnings and Precautions (5.1)].

Immune-Mediated Reactions

Immune-mediated reactions presenting as proteinuria, nephrotic syndrome, and necrotizing skin lesions have occurred in some patients following LUMIZYME treatment. Monitor patients for the development of systemic immune-mediated reactions involving skin and other organs while receiving LUMIZYME [see Warnings and Precautions (5.3)].

Risk of Acute Cardiorespiratory Failure

Infantile-onset Pompe disease (IOPD) patients with compromised cardiac or respiratory function may be at risk of serious acute exacerbation of their cardiac or respiratory compromise due to fluid overload and require additional monitoring [see Warnings and Precautions (5.4)].

1 INDICATIONS AND USAGE

LUMIZYME® is a hydrolytic lysosomal glycogen-specific enzyme indicated for patients with Pompe disease (acid α-glucosidase [GAA] deficiency).

2 DOSAGE AND ADMINISTRATION

2.1 Recommendations prior to LUMIZYME Treatment

- Administration of LUMIZYME should be supervised by a healthcare provider knowledgeable in the management of hypersensitivity reactions including anaphylaxis [see Warnings and Precautions (5.1)].
- Initiate LUMIZYME in a healthcare setting with appropriate medical monitoring and support measures, including access to cardiopulmonary resuscitation equipment [see Warnings and Precautions (5.1)].
- Prior to LUMIZYME administration, consider pretreating with antihistamines, antipyretics, and/or corticosteroids [see Warnings and Precautions (5.1, 5.2)].
- LUMIZYME must be reconstituted and diluted prior to use [see Dosage and Administration (2.3)].
- Appropriate medical monitoring and support measures, including cardiopulmonary resuscitation equipment, should be readily available during LUMIZYME administration [see Warnings and Precautions (5.1)].

2.2 Recommended Dosage and Administration

- The recommended dosage of LUMIZYME is 20 mg/kg body weight administered every 2 weeks as an intravenous infusion. The initial infusion rate should be no more than 1 mg/kg/hour [see Dosage and Administration (2.5)].

Missed Dose

If one or more doses are missed, restart LUMIZYME treatment as soon as possible, maintaining the 2-week interval between infusions thereafter.

2.3 Reconstitution and Dilution Instructions

Reconstitute and dilute LUMIZYME in the following manner.

Use aseptic technique during preparation. Do not use filter needles during preparation.

Reconstitute the Lyophilized Powder

- Determine the number of LUMIZYME vials to be reconstituted based on the actual body weight in kg and the recommended dose of 20 mg/kg. Round the number of vials up to the next whole number.
- Remove the required number of LUMIZYME vials from the refrigerator and allow the vials to sit for approximately 30 minutes at room temperature 20°C to 25°C (68°F to 77°F) prior to reconstitution.
- Reconstitute each vial by slowly injecting 10.3 mL of Sterile Water for Injection, down the inside wall of each vial. Avoid adding the Sterile Water for Injection to the vial forcefully or directly onto the lyophilized powder to minimize foaming.
- Gently tilt and roll each vial. Do not invert, swirl, or shake the vial. Each vial will yield a concentration of 5 mg/mL of LUMIZYME. The total extractable dose per vial is 50 mg per 10 mL.
- Visually inspect the reconstituted solution in the vials for particulate matter and discoloration. Discard if particles are present or the solution is discolored. The reconstituted solution may occasionally contain some LUMIZYME particles (typically less than 10 in a vial) in the form of thin white strands or translucent fibers subsequent to the initial inspection. This may also happen following dilution for infusion. These particles have been shown to contain LUMIZYME and may appear after the initial reconstitution step and increase over time. Studies have shown that these particles are removed via in-line filtration without having a detectable effect on the purity or strength.

Dilute the Reconstituted Solution

- Select and prepare an appropriate size 0.9% Sodium Chloride for Injection infusion bag with quantity sufficient of 0.9% Sodium Chloride for Injection to obtain the recommended total infusion volume per table 1 based on patient weight and dilute.
- Slowly withdraw the required volume of reconstituted solution from the LUMIZYME vial(s). Avoid foaming in the syringe. Discard any unused reconstituted solution remaining in the vial.
- Remove airspace from the prepared 0.9% Sodium Chloride for Injection infusion bag to minimize particle formation due to the sensitivity of LUMIZYME to air-liquid interfaces.
- Inject the LUMIZYME reconstituted solution slowly and directly into the port of the prepared 0.9% Sodium Chloride for Injection infusion bag. Avoid foaming and introducing air in the infusion bag.
- Gently invert or massage the infusion bag to mix the solution. Do not shake. After dilution, the solution will have a final concentration of 0.5 to 4 mg/mL of LUMIZYME.

2.4 Storage Instructions for the Reconstituted and Diluted Product

- The reconstituted and diluted solution should be administered without delay. Storage of the reconstituted solution at room temperature is not recommended.
- If immediate use is not possible, the reconstituted and diluted solution is stable for up to 24 hours refrigerated at 2°C to 8°C (36°F to 46°F).
- The reconstituted and diluted LUMIZYME solution should be protected from light.
- Do not freeze or shake.

2.5 Administration Instructions

- The total volume of infusion is determined by the patient's body weight and should be administered over approximately 4 hours.
- Administer LUMIZYME using an in-line low protein binding 0.2-micron filter.
- Infusions should be administered in a step-wise manner using an infusion pump. The initial infusion rate should be no more than 1 mg/kg/hr. The infusion rate may be increased by 2 mg/kg/hr every 30 minutes, after patient tolerance to the infusion rate is established, until a maximum rate of 7 mg/kg/hr is reached.
- Vital signs should be obtained at the end of each step. If the patient is stable, LUMIZYME may be administered at the maximum rate of 7 mg/kg/hr until the infusion is completed.
- The infusion rate may be slowed or temporarily stopped in the event of mild to moderate hypersensitivity reactions. In the event of anaphylaxis or severe hypersensitivity reaction, immediately discontinue administration of LUMIZYME and initiate appropriate medical treatment. See Table 1 below for the rate of infusion at each step, expressed as mL/hr based on the recommended infusion volume by patient weight.
- Do not infuse LUMIZYME in the same intravenous line with other products. Discard any unused product.

Table 1: Recommended LUMIZYME Infusion Volumes and Incremental Rate Steps by Patient Weight
Patient Weight Range | Total infusion volume | Step 1 1 mg/kg/hr | Step 2 3 mg/kg/hr | Step 3 5 mg/kg/hr | Step 4 7 mg/kg/hr
Patient Weight Range | Total infusion volume | Infusion Rate in mL/hr
1.25 to 2.5 kg | 25 mL | 1.25 | 3.75 | 6.25 | 6.6
2.6 to 10 kg | 50 mL | 3 | 8 | 13 | 18
10.1 to 20 kg | 100 mL | 5 | 15 | 25 | 35
20.1 to 30 kg | 150 mL | 8 | 23 | 38 | 53
30.1 to 35 kg | 200 mL | 10 | 30 | 50 | 70
35.1 to 50 kg | 250 mL | 13 | 38 | 63 | 88
50.1 to 60 kg | 300 mL | 15 | 45 | 75 | 105
60.1 to 100 kg | 500 mL | 25 | 75 | 125 | 175
100.1 to 120 kg | 600 mL | 30 | 90 | 150 | 210
120.1 to 140 kg | 700 mL | 35 | 105 | 175 | 245
140.1 to 160 kg | 800 mL | 40 | 120 | 200 | 280
160.1 to 180 kg | 900 mL | 45 | 135 | 225 | 315
180.1 to 200 kg | 1,000 mL | 50 | 150 | 250 | 350

3 DOSAGE FORMS AND STRENGTHS

For injection: 50 mg of LUMIZYME is supplied as a sterile, nonpyrogenic, white to off-white, lyophilized cake or powder in a single-dose vial for reconstitution. After reconstitution, the resultant solution concentration is 5 mg/mL.

4 CONTRAINDICATIONS

None.

5 WARNINGS AND PRECAUTIONS

5.1 Hypersensitivity Reactions Including Anaphylaxis

Hypersensitivity Reactions Including Anaphylaxis

Hypersensitivity reactions including anaphylaxis have been observed in patients during and up to 3 hours after a LUMIZYME infusion. Some of the hypersensitivity reactions were life-threatening and included anaphylactic shock, cardiac arrest, respiratory arrest, respiratory distress, hypoxia, apnea, dyspnea, bradycardia, tachycardia, bronchospasm, throat tightness, hypotension, angioedema (including tongue or lip swelling, periorbital edema, and face edema), and urticaria. Other accompanying reactions included chest discomfort/pain, wheezing, tachypnea, cyanosis, decreased oxygen saturation, convulsions, pruritus, rash, hyperhidrosis, nausea, dizziness, hypertension/increased blood pressure, flushing/feeling hot, erythema, pyrexia, pallor, peripheral coldness, restlessness, nervousness, headache, back pain, and paresthesia. Some of these reactions were IgE-mediated.

In clinical trials, hypersensitivity reactions including anaphylaxis were managed with infusion interruption; decreased infusion rate; and administration of antihistamines, corticosteroids, intravenous fluids, and/or oxygen. In some cases of anaphylaxis, epinephrine was administered. Some LUMIZYME-treated patients who experienced a hypersensitivity reaction and who tested positive for alglucosidase alfa-specific IgE antibodies were successfully rechallenged with a slower infusion rate at a lower dosage of LUMIZYME and continued to receive LUMIZYME under close clinical supervision. Because LUMIZYME-treated patients who develop anti-IgE alglucosidase alfa antibodies appear to be at a higher risk for developing hypersensitivity reactions including anaphylaxis, these patients should be monitored more closely during LUMIZYME administration.

Recommendations to Prevent, Mitigate, and Monitor for Hypersensitivity Reactions

Prior to LUMIZYME administration, consider pretreating with antihistamines, antipyretics, and/or corticosteroids. Administration of LUMIZYME should be supervised by a healthcare provider knowledgeable in the management of hypersensitivity reactions including anaphylaxis. Anaphylaxis has occurred during the early course of enzyme replacement therapy and after extended duration of therapy. Initiate LUMIZYME in a healthcare setting with appropriate medical monitoring and support measures, including access to cardiopulmonary resuscitation equipment.

- If a severehypersensitivity reaction (e.g., anaphylaxis) occurs, discontinue LUMIZYME and immediately initiate appropriate medical treatment, including use of epinephrine.
- If a mild or moderate hypersensitivity reaction occurs, consider temporarily holding the LUMIZYME infusion or slowing the infusion rate.

Consider the risks and benefits of readministering LUMIZYME following a hypersensitivity reaction including anaphylaxis. Patients may be rechallenged using slower infusion rates at a lower dosage than the recommended dosage [see Adverse Reactions (6.2)]. Inform patients of the symptoms of life-threatening hypersensitivity reactions, including anaphylaxis and recommend they seek immediate medical care should these symptoms occur.

5.2 Infusion-Associated Reactions

Infusion-associated reactions (IARs) such as pyrexia, chills, flu-like illness, myalgia, arthralgia, pain, fatigue, urticaria, rash, pruritus, erythema, dyspnea, tachycardia, flushing, nausea, headache and syncope occurred in LUMIZYME-treated patients [see Adverse Reactions (6.2)].

If an IAR occurs, decreasing the infusion rate, temporarily stopping the infusion, and/or administering antihistamines and/or antipyretics may ameliorate the symptoms. Closely monitor patients who have experienced IARs when re-administering LUMIZYME.

5.3 Immune-Mediated Reactions

Immune-mediated cutaneous reactions have been reported with LUMIZYME including necrotizing skin lesions [see Adverse Reactions (6.2)]. Systemic immune-mediated reactions, including possible type III immune-mediated reactions have been observed with LUMIZYME. These reactions occurred several weeks to 3 years after initiation of LUMIZYME infusions. Skin biopsy in one patient demonstrated deposition of anti-rhGAA antibodies in the lesion. Another patient developed severe inflammatory arthropathy in association with pyrexia and elevated erythrocyte sedimentation rate. Nephrotic syndrome secondary to membranous glomerulonephritis was observed in some LUMIZYME-treated patients with Pompe disease who had persistently positive anti-rhGAA IgG antibody titers. In these patients, renal biopsy was consistent with immune complex deposition. Patients improved following LUMIZYME treatment interruption [see Adverse Reactions (6.2)].

LUMIZYME treated patients should be monitored for the development of systemic immune-mediated reactions involving skin and other organs including periodic urinalysis. If immune-mediated reactions occur, consider discontinuing the LUMIZYME administration, and initiating appropriate medical treatment. The risks and benefits of readministering LUMIZYME following an immune-mediated reaction should be considered. Some patients have been able to be rechallenged and have continued to receive LUMIZYME under close clinical supervision. Immune tolerance induction administered in conjunction with LUMIZYME may also aide tolerability of LUMIZYME under the management of a clinical specialist knowledgeable in immune tolerance induction in pediatric patients with IOPD or LOPD.

5.4 Risk of Acute Cardiorespiratory Failure

Patients with acute underlying respiratory illness or compromised cardiac and/or respiratory function may be at risk of serious exacerbation of their cardiac or respiratory compromise during infusions. Appropriate medical support and monitoring measures should be readily available during LUMIZYME infusion, and some patients may require prolonged observation times that should be individualized based on the needs of the patient. Acute cardiorespiratory failure has been observed in infantile-onset Pompe disease patients with underlying cardiac hypertrophy, possibly associated with fluid overload with intravenous administration of LUMIZYME [see Dosage and Administration (2.2)].

5.5 Risk of Cardiac Arrhythmia and Sudden Cardiac Death during General Anesthesia for Central Venous Catheter Placement

Administration of general anesthesia can be complicated by the presence of severe cardiac and skeletal (including respiratory) muscle weakness. Therefore, caution should be used when administering general anesthesia. Ventricular arrhythmias and bradycardia, resulting in cardiac arrest or death, or requiring cardiac resuscitation or defibrillation have been observed in patients with IOPD with cardiac hypertrophy during general anesthesia for central venous catheter placement.

5.6 Risk of Developing Anti-alglucosidase Alfa Antibodies

As shown from clinical trials and published literature, individualized immune tolerance induction regimen administered prior to and with initiation of LUMIZYME has been reported to aid tolerability of LUMIZYME and reduce the development of high ADA titers in CRIM-negative IOPD patients. Furthermore, CRIM status has been shown to be associated with immunogenicity and patients' responses to LUMIZYME. LUMIZYME-treated infants with IOPD who are CRIM-negative (indicating no endogenous enzyme is detected) have shown poorer clinical response (loss of motor function, ventilator dependence, or death) in the presence of high sustained IgG ADA titers and positive inhibitory antibodies compared to CRIM-positive infants [see Adverse Reactions (6.2)]. However, high and sustained ADA titers has also occurred in a limited number of CRIM-positive patients, generally with very low endogenous enzyme [see Clinical Pharmacology (12.6)]. Therefore, these patients must be managed by a clinical specialist knowledgeable in immune tolerance induction in Pompe disease.

Some alglucosidase alfa-treated patients who developed high sustained IgG ADA titers had reduced efficacy. Some alglucosidase alfa-treated patients with high IgG ADA titers had a higher incidence of IARs.

Patients with IOPD should have a cross-reactive immunologic material (CRIM) assessment early in their disease course.

Anti-alglucosidase alfa antibody (referred to as ADA) titers should be obtained during LUMIZYME treatment. Contact Genzyme Corporation at 1-800-745-4447 for information on ADA testing.

Recommend the following ADA testing:

- Baseline serum ADA sample collection prior to the first LUMIZYME infusion is strongly encouraged.
- For patients with:
  - IOPD, suggest regular ADA monitoring during first year of treatment (example: every 3 months).
  - LOPD, suggest ADA be monitored within six months of LUMIZYME initiation with subsequent monitoring as clinically warranted based on safety and efficacy considerations.
- If patients [see Adverse Reactions (6.2) and Clinical Pharmacology (12.6)]:
  - Develop hypersensitivity reactions, consider testing for IgG ADA, IgE ADA and other mediators.
  - Develop immune-mediated reactions that are not hypersensitivity reactions, consider testing for IgG ADA.
  - Lose or have a reduced clinical response, consider testing for IgG ADA and for inhibitory antibody activity.

6 ADVERSE REACTIONS

The following serious adverse reactions are described below and elsewhere in the labeling:

- Hypersensitivity Reactions Including Anaphylaxis [see Warnings and Precautions (5.1)]

6.1 Clinical Trials Experience

Because clinical trials are conducted under widely varying conditions, adverse reaction rates observed in the clinical trials of a drug cannot be directly compared to rates in the clinical trials of another drug and may not reflect the rates observed in clinical practice.

In clinical trials, the most common adverse reactions (≥5%) following intravenous alglucosidase alfa treatment were hypersensitivity reactions, and included anaphylaxis, rash, pyrexia, flushing/feeling hot, urticaria, headache, hyperhidrosis, nausea, cough, decreased oxygen saturation, tachycardia, tachypnea, chest discomfort, dizziness, muscle twitching, agitation, cyanosis, erythema, hypertension/increased blood pressure, pallor, rigors, tremor, vomiting, fatigue, and myalgia.

Adverse Reactions in Clinical Trials in Infantile-Onset and Juvenile-Onset Pompe Disease

Two multicenter, open-label clinical trials (Trials 1 and 2) [see Clinical Studies (14.1)] were conducted in 39 patients with infantile-onset Pompe disease (IOPD), aged 1 month to 3.5 years old. Approximately half of the patients (54%) were male. Patients were treated with intravenous alglucosidase alfa 20 or 40 mg/kg every other week for periods ranging from 1 to 106 weeks (mean: 61 weeks).

The most serious adverse reactions reported with alglucosidase alfa treatment included anaphylaxis and acute cardiorespiratory failure.

The most common adverse reactions requiring intervention in these clinical trials were hypersensitivity reactions, that occurred in 20 of 39 (51%) patients treated with alglucosidase alfa, and included rash, pyrexia, urticaria, flushing, decreased oxygen saturation, cough, tachypnea, tachycardia, hypertension/increased blood pressure, pallor, rigors, vomiting, cyanosis, agitation, and tremor. These reactions were more likely to occur with higher infusion rates or doses. Some patients who were pretreated with antihistamines, antipyretics and/or corticosteroids still experienced hypersensitivity reactions.

Table 2 summarizes all adverse reactions that occurred in ≥5% of patients (2 or more patients) treated with alglucosidase alfa in clinical trials described above.

Table 2: Adverse Reactions that Occurred in at Least 5% of Alglucosidase Alfa-Treated Infantile-Onset Patients in Trials 1 and 2
 | Number of Patients (N=39) n (%)
Adverse Reaction | 20 (51)
Rash (including rash erythematous, rash macular and maculopapular) | 7 (18)
Pyrexia | 6 (15)
Urticaria | 5 (13)
Flushing | 5 (13)
Hypertension/Increased Blood Pressure | 4 (10)
Decreased Oxygen Saturation | 3 (8)
Cough | 3 (8)
Tachypnea | 3 (8)
Tachycardia | 3 (8)
Erythema | 2 (5)
Vomiting | 2 (5)
Rigors | 2 (5)
Pallor | 2 (5)
Cyanosis | 2 (5)
Agitation | 2 (5)
Tremor | 2 (5)

An open-label, single-center trial (Trial 3) was conducted in 18 treatment-naive patients with IOPD who were treated with alglucosidase alfa [see Clinical Studies (14.1)]. Adverse reactions observed in these patients were similar to patients with IOPD who received alglucosidase alfa in other clinical trials.

Additional hypersensitivity reactions observed in patients with IOPD treated with alglucosidase alfa in other clinical trials and expanded access programs included livedo reticularis, irritability, retching, increased lacrimation, ventricular extrasystoles, nodal rhythm, rales, respiratory tract irritation, and cold sweat.

Safety was also evaluated in 99 patients (51 male, 48 females) with Pompe disease in an ongoing, open-label, prospective study in patients 12 months of age and older who were previously treated with another alglucosidase alfa product and switched to LUMIZYME. Patients were aged 1 to 18 years with a median duration of treatment of 437 days (range 13 to 466 days). No new safety findings were observed following the switch to 4000 L scale of alglucosidase alfa.

Adverse Reactions in Clinical Trials in Late-Onset Pompe Disease

Assessment of adverse reactions in patients with late-onset Pompe disease (LOPD) is based on the exposure of 90 patients (45 male, 45 female), aged 10 to 70 years, to intravenous infusions of 20 mg/kg alglucosidase alfa or placebo in a randomized, double-blind, placebo-controlled trial (Trial 4). All patients were naive to enzyme replacement therapy. Patients were randomized in a 2:1 ratio and received intravenous alglucosidase alfa or placebo every other week for 78 weeks (18 months). Two patients who received alglucosidase alfa discontinued the trial due to anaphylactic reactions.

Serious adverse reactions reported with alglucosidase alfa included anaphylaxis, which presented as angioedema, throat tightness and chest pain/discomfort. One patient with a history of Wolff-Parkinson-White syndrome experienced a serious adverse reaction of supraventricular tachycardia.

The most common adverse reactions (≥3%; 2 or more patients) observed in alglucosidase alfa-treated patients were hypersensitivity reactions and included anaphylaxis, headache, nausea, urticaria, dizziness, chest discomfort, vomiting, hyperhidrosis, flushing/feeling hot, increased blood pressure, paresthesia, pyrexia, local swelling, diarrhea, pruritus, rash, and throat tightness.

Delayed-onset reactions, defined as adverse reactions that occurred 2 to 48 hours after completion of alglucosidase alfa infusion, that were observed in ≥3% more patients in the alglucosidase alfa-treated group compared to patients in the placebo-treated group in the controlled trial, included hyperhidrosis. Additional delayed-onset reactions that occurred in alglucosidase alfa-treated patients included fatigue, myalgia, and nausea.

Table 3 summarizes the most common adverse reactions that occurred in at least 3% of alglucosidase alfa-treated patients and with a higher incidence than the placebo-treated patients in Trial 4 (patients with LOPD).

Table 3: Adverse Reactions in Patients with LOPD (Trial 4) [Adverse reactions that occurred in ≥3% of alglucosidase alfa-treated patients and with a higher incidence than placebo-treated patients]
Adverse Reaction | Alglucosidase Alfa n=60 N (%) | Placebo n=30 N (%)
Hyperhidrosis | 5 (8.3) | 0 (0)
Urticaria | 5 (8.3) | 0 (0)
Anaphylaxis | 4 (6.7) | 0 (0)
Chest Discomfort | 4 (6.7) | 1 (3.3)
Muscle Twitching | 4 (6.7) | 1 (3.3)
Myalgia | 3 (5.0) | 1 (3.3)
Flushing/Feeling Hot | 3 (5.0) | 0 (0)
Increased Blood Pressure | 3 (5.0) | 0 (0)
Vomiting | 3 (5.0) | 0 (0)
Edema, Peripheral | 2 (3.3) | 0 (0)
Pruritus | 2 (3.3) | 0 (0)
Rash Papular | 2 (3.3) | 0 (0)
Throat Tightness | 2 (3.3) | 0 (0)

6.2 Postmarketing Experience

The following adverse reactions have been identified during post approval use of alglucosidase alfa. Because these reactions are reported voluntarily from a population of uncertain size, it is not always possible to reliably estimate their frequency or establish a causal relationship to drug exposure.

In the postmarketing experience with LUMIZYME, serious adverse reactions have been reported, including anaphylaxis [see Boxed Warning and Warnings and Precautions (5.1)]. Acute cardiorespiratory failure, possibly associated with fluid overload, has been reported in infantile-onset Pompe disease patients with pre-existing hypertrophic cardiomyopathy [see Boxed Warning and Warning and Precautions (5.3)].

Infusion associated reactions, including pyrexia, chills, fatigue, urticaria, rash, pruritus, erythema, dyspnea, hypotension, bradycardia, tachycardia, flushing, nausea, headache, and syncope have been reported with alglucosidase alfa.

In addition to the hypersensitivity reactions reported in clinical trials [see Adverse Reactions (6.1)], the following hypersensitivity reactions have been reported in at least 2 patients and included: anaphylactic shock, respiratory failure, respiratory arrest, cardiac arrest, hypoxia, dyspnea, wheezing, convulsions, peripheral coldness, restlessness, nervousness, back pain, stridor, pharyngeal edema, abdominal pain, apnea, muscle spasm, and conjunctivitis. In addition, one case of hyperparathyroidism has been reported.

Systemic and cutaneous immune-mediated reactions, including proteinuria and nephrotic syndrome secondary to membranous glomerulonephritis, and necrotizing skin lesions have been reported in postmarketing safety experience with alglucosidase alfa [see Warnings and Precautions (5.2)].

8 USE IN SPECIFIC POPULATIONS

8.1 Pregnancy

Pregnancy Exposure Registry

There is a pregnancy exposure registry that monitors pregnancy outcomes in women exposed to LUMIZYME during pregnancy. Pregnant women and women of reproductive potential should be encouraged to enroll in the Pompe patient registry. The registry will monitor the effect of LUMIZYME on pregnant women and their offspring. For more information, visit www.registrynxt.com or call 1-800-745-4447, extension 15500.

Risk Summary

Data from postmarketing reports and published case reports with alglucosidase alfa use in pregnant women have not identified a LUMIZYME-associated risk of major birth defects, miscarriage, or adverse maternal or fetal outcomes. The continuation of treatment for Pompe disease during pregnancy should be individualized to the pregnant woman. Untreated Pompe disease may result in worsening disease symptoms in pregnant women (see Clinical Considerations).

Reproduction studies performed in mice and rabbits at doses resulting in exposures up to 0.4 or 0.5 times the human steady-state AUC (area under the plasma concentration-time curve), respectively, during the period of organogenesis revealed no evidence of effects on embryo-fetal development. In mice there was an increase in pup mortality during lactation at maternal exposures 0.4 times the human steady-state AUC (see Data).

The background risk of major birth defects and miscarriage in the indicated population is unknown. All pregnancies have a background risk of birth defect, loss or other adverse outcomes. In the U.S. general population, the estimated background risk of major birth defects and miscarriage in clinically recognized pregnancies is 2% to 4% and 15% to 20%, respectively.

Clinical Considerations

Disease-associated Maternal and/or Embryo-fetal Risk

Untreated Pompe disease has been associated with worsening respiratory and musculoskeletal symptoms in some pregnant women.

Data

Animal Data

All reproductive studies included pretreatment with diphenhydramine to prevent or minimize hypersensitivity reactions. The effects of alglucosidase alfa were evaluated based on comparison to a control group treated with diphenhydramine alone. Daily intravenous administration of alglucosidase alfa up to 40 mg/kg in mice and rabbits (0.4 and 0.5 times the human steady-state AUC, respectively, at the recommended biweekly dose) during the period of organogenesis had no effects on embryo-fetal development. Administration of 40 mg/kg intravenously every other day in mice (0.4 times the human steady-state AUC at the recommended biweekly dose) during the period of organogenesis through lactation produced an increase in mortality of offspring during the lactation period.

8.2 Lactation

Risk Summary

Available published literature suggests the presence of alglucosidase alfa in human milk. There are no reports of adverse effects of alglucosidase alfa on the breastfed infant. There is no information on the effects of alglucosidase alfa on milk production. The developmental and health benefits of breastfeeding should be considered along with the mother's clinical need for LUMIZYME and any potential adverse effects on the breastfed child from LUMIZYME or from the underlying maternal condition.

Lactating women with Pompe disease treated with LUMIZYME should be encouraged to enroll in the Pompe disease registry [see Use in Specific Populations (8.1)].

Clinical Considerations

A lactating woman may consider interrupting breastfeeding, pumping and discarding breast milk during treatment and for 24 hours after LUMIZYME administration in order to minimize drug exposure to a breastfed infant.

8.4 Pediatric Use

The safety and effectiveness of LUMIZYME has been established in pediatric patients with Pompe disease [see Adverse Reactions (6.2)].The use of LUMIZYME for this pediatric indication is supported by evidence from an adequate and well-controlled trial in 57 treatment-naive pediatric patients with IOPD treated with alglucosidase alfa, aged 0.2 month to 3.5 years at first infusion, (Trials 1, 2, and 3) [see Clinical Studies (14.1)] and 90 adult and pediatric patients with LOPD in a randomized, double-blind, placebo-controlled trial including 2 patients 16 years of age or less [see Clinical Studies (14.2)].

Anaphylaxis, hypersensitivity reactions, and acute cardiorespiratory failure have occurred in pediatric patients [see Boxed Warning, Warnings and Precautions (5.1, 5.3)]. Additionally, cardiac arrhythmia and sudden cardiac death have occurred in pediatric patients during general anesthesia for central venous catheter placement [see Warnings and Precautions (5.4)].

8.5 Geriatric Use

The randomized, double-blind, placebo-controlled study of alglucosidase alfa did not include sufficient numbers (n=4) of patients aged 65 years and over to determine whether they respond differently from younger adult patients [see Clinical Studies (14.1)].

11 DESCRIPTION

Alglucosidase alfa is a hydrolytic lysosomal glycogen-specific enzyme encoded by the predominant of nine observed haplotypes of the human acid α-glucosidase (GAA) gene. Alglucosidase alfa is produced by recombinant DNA technology in a Chinese hamster ovary cell line. Alglucosidase alfa degrades glycogen by catalyzing the hydrolysis of α-1,4- and α-1,6- glycosidic linkages of lysosomal glycogen.

Alglucosidase alfa is a glycoprotein with a calculated mass of 99,377 Daltons for the polypeptide chain, and a total mass of approximately 109,000 Daltons, including carbohydrates. Alglucosidase alfa has a specific activity of 3.6 to 5.4 units/mg (one unit is defined as that amount of activity that results in the hydrolysis of 1 micromole of synthetic substrate per minute under specified assay conditions). Alglucosidase alfa is intended for intravenous infusion. It is supplied as a sterile, nonpyrogenic, white to off-white, lyophilized cake or powder for reconstitution with 10.3 mL Sterile Water for Injection, USP. Each 50 mg vial contains 52.5 mg alglucosidase alfa, 210 mg mannitol, 0.5 mg polysorbate 80, 9.9 mg sodium phosphate dibasic heptahydrate, and 31.2 mg sodium phosphate monobasic monohydrate. Following reconstitution as directed, each vial contains 10.5 mL reconstituted solution and a total extractable volume of 10 mL at 5 mg/mL alglucosidase alfa. Alglucosidase alfa does not contain preservatives; each vial is for single dose only.

12 CLINICAL PHARMACOLOGY

12.1 Mechanism of Action

Pompe disease (acid maltase deficiency, glycogen storage disease type II, GSD II, glycogenosis type II) is an inherited disorder of glycogen metabolism caused by the absence or marked deficiency of the lysosomal enzyme GAA.

Alglucosidase alfa provides an exogenous source of GAA. Binding to mannose-6-phosphate receptors on the cell surface has been shown to occur via carbohydrate groups on the GAA molecule, after which it is internalized and transported into lysosomes, where it undergoes proteolytic cleavage that results in increased enzymatic activity. It then exerts enzymatic activity in cleaving glycogen.

12.2 Pharmacodynamics

Clinical pharmacodynamic studies have not been conducted for alglucosidase alfa.

12.3 Pharmacokinetics

The pharmacokinetics of alglucosidase alfa was evaluated in 13 patients with infantile-onset Pompe disease, aged 1 month to 7 months, who received 20 mg/kg (approximately as a 4-hour infusion) or 40 mg/kg (approximately as a 6.5-hour infusion) of alglucosidase alfa every 2 weeks. The measurement of alglucosidase alfa plasma concentration was based on an activity assay using an artificial substrate. Systemic exposure was approximately dose proportional between the 20 and 40 mg/kg doses. Based on the pharmacokinetic blood samples collected for 12 hours after a 4-hour intravenous infusion of 20 mg/kg (n=5), the estimated mean AUC was 811 mcg∙hr/mL with 17% coefficient of variation [CV], Cmax was 162 mcg/mL with 19% CV, clearance was 25 mL/hr/kg with 16% CV, and half-life was 2.3 hours with 17% CV.

The pharmacokinetics of alglucosidase alfa was also evaluated in a separate trial of 14 patients with infantile-onset Pompe disease, aged 6 months to 3.5 years, who received 20 mg/kg of alglucosidase alfa as a 4-hour infusion every 2 weeks. The pharmacokinetic parameters were similar to those observed for the infantile-onset Pompe disease patients aged 1 month to 7 months who received the 20 mg/kg dose.

The pharmacokinetics of alglucosidase alfa was evaluated in another trial of 10 adult and 10 pediatric patients with Pompe disease who received a single dose of 20 mg/kg of alglucosidase alfa as a 4-hour infusion. In pediatric patients, aged 7 months to 13.7 years, the estimated mean AUC was 1,110 mcg∙hr/mL with 68% CV and Cmax was 204 mcg/mL with 46% CV. In adult patients, aged 19 to 57 years, the estimated mean AUC was 1,890 mcg∙hr/mL with 51% CV and Cmax was 307 mcg/mL with 47% CV.

12.6 Immunogenicity

The observed incidence of anti-drug antibodies (ADA) is highly dependent on the sensitivity and specificity of the assay. Differences in assay methods preclude meaningful comparisons of the incidence of ADAs in the studies described below with the incidence of ADAs in other studies, including those of LUMIZYME or of other alglucosidase alfa products.

Immunogenicity in Patients with Infantile-onset Pompe Disease

Thirty-nine patients with infantile-onset Pompe disease (IOPD), aged 1 month to 3.5 years, were treated with 20 or 40 mg/kg of intravenous alglucosidase alfa every other week for periods that ranged from 1 to 106 weeks (mean: 61 weeks) in two open-label clinical trials (Trials 1 and 2) [see Clinical Studies (14.1, 14.2)]. In Trials 1 and 2, 34/38 (89%) of alglucosidase alfa-treated patients tested positive for anti-alglucosidase alfa antibodies (referred to as ADA).

Immunogenicity in Patients with Late-onset Pompe Disease

Ninety patients with late-onset Pompe disease (LOPD), aged 10 to 70 years, were administered 20 mg/kg of intravenous alglucosidase alfa or intravenous placebo every other week (2:1 ratio) for 78 weeks in a randomized, double-blinded, placebo-controlled trial (Trial 4) [see Clinical Studies (14.2)]. In Trial 4, 59/59 (100%) of alglucosidase alfa-treated patients with available samples developed ADA. These patients were all cross-reactive immunologic material (CRIM) positive. Most patients who developed ADA did so within the first three months of exposure (median time to seroconversion was four weeks).

Antibody titers for cellular uptake inhibition were present in 18 of 59 (31%) alglucosidase alfa-treated patients by Week 78. Patients who tested positive for cellular uptake inhibition tended to have higher IgG titers than patients who tested negative for cellular uptake inhibition. None of the 59 evaluable patients tested positive for inhibition of enzyme activity.

Immunogenicity in Patients with Infantile-onset Pompe Disease or Late-onset Pompe Disease

Some patients with IOPD or LOPD who were ADA positive in Trials 1, 2 and 4 tested positive for inhibition of enzyme activity and/or uptake in in vitro assays. However, the clinical relevance of this in vitro inhibition is unclear.

Negative CRIM status (indicating no endogenous enzyme is detected) is a risk factor for LUMIZYME-treated patients to develop high and sustained ADA titers. However, high and sustained ADA titers have also occurred in a limited number of CRIM-positive patients, generally with very low endogenous enzyme.

Anti-Drug Antibody Effects on Pharmacokinetics

In Trials 1 and 2, 19 of 21 (90%) alglucosidase alfa-treated patients with IOPD - who had pharmacokinetics (PK) and antibody titer data available at Week 12 - developed ADA. Of these 19 patients, 5 patients with antibody titers ≥12,800 at Week 12 had a 50% mean increase in clearance (range 5% to 90%) from Week 1 to Week 12, while the 14 patients with antibody titers <12,800 at Week 12 had no significant change in the mean clearance values at Week 1 and Week 12.

In Trial 4, 5/32 (16%) of alglucosidase alfa-treated patients with LOPD that had evaluable PK samples tested positive for cellular uptake inhibition. An approximately 1.2-fold to 1.8- fold greater clearance was observed at Week 52 in 4 of 5 patients that tested positive for antibodies that inhibit the cellular uptake of enzyme in an in vitro assay compared to Week 0. PK in 4 of these 5 patients over time indicated an increase in clearance with increase in IgG titer.

Anti-Drug Antibody Effects on Safety and Efficacy

A small number of alglucosidase alfa-treated patients with LOPD who tested positive for alglucosidase alfa-specific IgE antibodies experienced anaphylactic reactions [see Warnings and Precautions (5.1)].

Some alglucosidase alfa-treated patients who developed high sustained ADA titers had reduced efficacy. Furthermore, CRIM-negative infants have shown reduced clinical effect in the presence of high sustained ADA titers with inhibitory activity [see Warnings and Precautions (5.6)].

There was no identified clinically significant effect of high ADA titers on the development of IARs in LUMIZYME-treated patients.

13 NONCLINICAL TOXICOLOGY

13.1 Carcinogenesis, Mutagenesis, Impairment of Fertility

Long-term studies in animals to evaluate carcinogenic potential or studies to evaluate mutagenic potential have not been performed with alglucosidase alfa.

Intravenous administration of alglucosidase alfa every other day in mice at doses up to 40 mg/kg (0.4 times the human AUC at the recommended biweekly dose) had no effect on fertility and reproductive performance.

14 CLINICAL STUDIES

14.1 Clinical Trials in Infantile-Onset Pompe Disease

The safety and effectiveness of alglucosidase alfa in the treatment patients with infantile-onset Pompe disease (IOPD) were assessed in 57 treatment-naive infantile-onset Pompe disease patients, aged 0.2 month to 3.5 years at first alglucosidase alfa infusion, in three separate open-label, single-arm clinical trials (Trials 1, 2, and 3).

Trial 1 (Patients with IOPD)

Trial 1 was an international, multicenter, open-label, clinical trial of 18 patients with IOPD. This trial was conducted between 2003 and 2005. Patients were randomized 1:1 to receive either 20 mg/kg or 40 mg/kg of intravenous alglucosidase alfa every two weeks, with length of treatment ranging from 52 to 106 weeks. Enrollment was restricted to patients 7 months of age or younger at first infusion with clinical signs of Pompe disease and cardiac hypertrophy, and who did not require ventilatory support at trial entry. Fourteen patients were cross reactive immunologic material (CRIM) positive, and 4 patients were CRIM negative.

Efficacy was assessed by comparing the proportions of alglucosidase alfa-treated patients who died or needed invasive ventilator support at 18 months of age with the mortality experience of a historical cohort of untreated patients with IOPD with similar age and disease severity. In the historical cohort, 61 untreated patients with IOPD diagnosed by age 6 months, born between 1982 and 2002, were identified by a retrospective review of medical charts. By 18 months of age, 15 of 18 (83%) alglucosidase alfa-treated patients were alive without invasive ventilatory support and 3 (17%) required invasive ventilator support, whereas only one of the 61 (2%) historical control patients was alive. No differences in outcome were observed between patients who received 20 mg/kg versus 40 mg/kg.

Other outcome measures in this trial included unblinded assessments of motor function by the Alberta Infant Motor Scale (AIMS), a measure of infant motor performance that assesses motor maturation of the infant through age 18 months. Although gains in motor function were noted in 13 patients, the motor function was substantially delayed compared to normal infants of comparable age in the majority of patients. Two of 9 patients who had initially demonstrated gains in motor function after 12 months of alglucosidase alfa treatment regressed despite continued treatment.

Changes from baseline to Month 12 in left ventricular mass index (LVMI), a measure of pharmacodynamic effect, were evaluated by echocardiography. Fifteen patients who underwent both baseline and Month 12 echocardiograms demonstrated decreases from baseline in LVMI (mean decrease 118 g/m^2, range 45 to 193 g/m^2). However, the magnitude of the decrease in LVMI did not correlate with the clinical outcome measure of ventilator-free survival.

Trial 2 (Patients with IOPD)

Trial 2 was an international, multicenter, non-randomized, open-label clinical trial that enrolled 21 patients with IOPD aged 3 months to 3.5 years at first infusion. Eighteen patients were CRIM positive and 3 patients were CRIM negative. All patients received intravenous 20 mg/kg alglucosidase alfa every other week for up to 104 weeks. Five of 21 patients were receiving invasive ventilatory support at the time of first infusion.

The primary outcome measure was the proportion of patients alive at the conclusion of treatment. At the 52-week interim analysis, 16 of 21 patients were alive. Sixteen patients were free of invasive ventilatory support at the time of first infusion; of these, 4 died, 2 required invasive ventilatory support, and 10 were free of invasive ventilatory support after 52 weeks of treatment. For the 5 patients who were receiving invasive ventilatory support at baseline, 1 died, and 4 remained on invasive ventilatory support at Week 52.

Trial 3 (Patients with IOPD)

Trial 3 was an open-label, single-center trial in 18 patients with IOPD who had a confirmed diagnosis of Pompe disease as identified through a newborn screening program. All patients were CRIM positive. Patients were treated with intravenous alglucosidase alfa prior to 6 months of age (0.2 to 5.8 months at first infusion). Sixteen patients reached 18 months of age at the time of analysis, and all (100%) were alive without invasive ventilator support.

14.2 Clinical Trials in Late-Onset Pompe Disease

The safety and efficacy of alglucosidase alfa were assessed in 90 patients with late-onset Pompe disease (LOPD), aged 10 to 70 years, in a randomized, double-blind, placebo-controlled trial (Trial 4). All patients were naive to enzyme replacement therapy. Patients were allocated in a 2:1 ratio and received 20 mg/kg of intravenous alglucosidase alfa (n=60) or intravenous placebo (n=30) every other week for 78 weeks (18 months).

The youngest alglucosidase alfa-treated patient was 16 years of age, and the youngest placebo-treated patient was 10 years of age. The trial population included 34 males and 26 females (n=60) in the alglucosidase alfa group and 11 males and 19 females (n=30) in the placebo group. At baseline, all patients were ambulatory (some required assistive walking devices), did not require invasive ventilator support or non-invasive ventilation while awake and sitting upright, and had a forced vital capacity (FVC) between 30 and 79% of predicted in the sitting position. Patients who could not walk 40 meters in 6 minutes or were unable to perform appropriate pulmonary and muscle function testing were excluded from the study.

A total of 81 of 90 patients completed the trial. Of the 9 patients who discontinued, 5 were in the alglucosidase alfa group and 4 were in the placebo group. Three patients discontinued the study due to an adverse event; two patients were in the alglucosidase alfa treatment group and one patient was in placebo group.

At trial entry, the mean % predicted FVC in the sitting position among all patients was about 55%. After 78 weeks, the mean % predicted FVC increased to 56.2% for alglucosidase alfa-treated patients and decreased to 52.8% for placebo-treated patients indicating an alglucosidase alfa treatment effect of 3.4% (95% confidence interval: [1.3% to 5.5%]; p=0.004). Stabilization of % predicted FVC in the alglucosidase alfa-treated patients was observed (see Figure 1).

Figure 1: Mean FVC Upright (% Predicted) Over Time in Patients with LOPD (Trial 4)

At trial entry, the mean 6 minute walk test (6MWT) among all patients was about 330 meters. After 78 weeks, the mean 6MWT increased by 25 meters for alglucosidase alfa-treated patients and decreased by 3 meters for placebo-treated patients indicating an alglucosidase alfa treatment effect of 28 meters (95% confidence interval: [-1 to 52 meters]; p=0.06) (see Figure 2).

Figure 2: Mean Six Minute Walk Test Total Distance Walked Over Time in Patients with LOPD (Trial 4)

16 HOW SUPPLIED/STORAGE AND HANDLING

LUMIZYME 50 mg vials are supplied as a sterile, nonpyrogenic, preservative-free, white to off-white lyophilized cake or powder in single-dose vials.

NDC 58468-0160-1 (Carton of one single-dose vial)

NDC 58468-0160-2 (Carton of ten single-dose vials)

STORAGE AND HANDLING

Store LUMIZYME under refrigeration between 2°C and 8°C (36°F and 46°F). Do not use LUMIZYME after the expiration date on the vial.

17 PATIENT COUNSELING INFORMATION

Hypersensitivity Reactions Including Anaphylaxis, Infusion-Associated Reactions (IARs) and Immune-Mediated Reactions

Advise the patient and caregiver that life-threatening hypersensitivity reactions, including anaphylaxis, IARs, and immune-mediated reactions may occur with LUMIZYME treatment.

Advise the patient and caregiver that anaphylaxis and immune-mediated reactions may occur during the early course of enzyme replacement therapy and after extended duration of therapy.

Inform the patient and caregiver of the symptoms of life-threatening hypersensitivity reactions including anaphylaxis, IARs, and immune-mediated reactions and have them seek immediate medical care should these symptoms occur [see Warning and Precautions (5.1, 5.2, 5.3)].

Risk of Acute Cardiorespiratory Failure

Advise the patient and caregiver that patients with underlying respiratory illness or compromised cardiac or respiratory function may be at risk of acute cardiorespiratory failure. Patients with compromised cardiac or respiratory function may require close observation during and after alglucosidase alfa administration.

Pompe Registry

Inform the patient and their caregiver(s) that the Pompe Registry has been established to better understand the variability and progression of Pompe disease, and to continue to monitor and evaluate long-term effects of LUMIZYME on pregnant women and their offspring [see Use in Specific Populations (8.1)]. Inform the patient and their caregiver(s) that their participation is voluntary and may involve long-term follow-up and to visit www.registrynxt.com or call 1-800-745-4447, extension 15500.

LUMIZYME is manufactured and distributed by:
Genzyme Corporation
Cambridge, MA 02141
1-800-745-4447 (phone)
A SANOFI COMPANY
U.S. License Number: 1596

LUMIZYME and GENZYME are registered trademarks of Genzyme Corporation.

PRINCIPAL DISPLAY PANEL - 50 mg Vial Carton

Lumizyme®
(alglucosidase alfa)

50 mg/vial

For Injection

For Intravenous Infusion Only

Rx only

Contains No Preservatives

SANOFI GENZYME